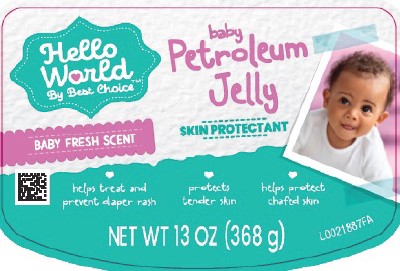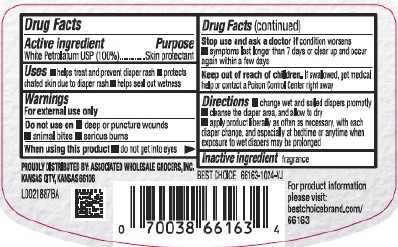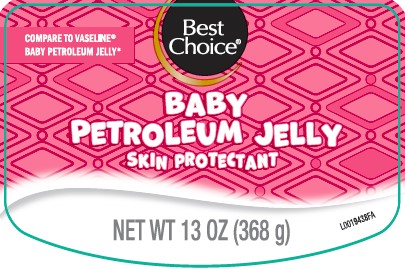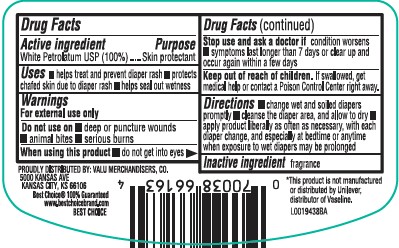 DRUG LABEL: Petroleum
NDC: 63941-340 | Form: JELLY
Manufacturer: Valu Merchandisers Company
Category: otc | Type: HUMAN OTC DRUG LABEL
Date: 20260216

ACTIVE INGREDIENTS: PETROLATUM 100 g/100 g

Best Choice_Hello World 519.001/519AD
Baby Petroleum Jelly

Active ingredient

White Petrolatum USP (100%)

Purpose

Skin protectant

Uses

- helps treat and prevent diaper rash
- protects chafed skin due to diaper rash
- helps seal out wetness

Warnings

For external use only

Do not use on

- deep or puncture wounds
- animal bites
- serious burns

When using this product

- do not get into eyes

Stop use and ask a doctor if

- condition worsens
- symptoms longer than 7 days or clear up and occur again within a few days

Keep out of reach of children.

If swallowed, get medical help or contact a Poison Control Center right away.

Directions

- change wet and soiled diapers promptly
- cleanse the diaper area, and allow to dry
- apply product liberally as often as necessary, with each diaper change, and especially at bedtime or anytime when exposure to wet diapers may be prolonged

Inactive ingredient

fragrance

Adverse reactions

PROUDLY DISTRIBUTED BY: ASSOCIATED WHOLESALE GROCERS, INC.

KANSAS CITY, KS 66106

Best Choice 66163-1024-VJ

For product information please visit:

bestchoicebrand.com/66163

Principal Panel Display

Best Choice®

COMPARE TO VASELINE®BABY PETROLEUM JELLY*

BABY PETROLEUM JELLY

SKIN PROTECTANT

NET WT 13 OZ (368 g)

Principal Panel Display

Hello World

By Best Choice ™

baby

Petroleum Jelly

BABY FRESH SCENT

SKIN PROTECTANT

- helps treat and prevent diaper rash
- protects tender skin
- helps protect chafed skin

NET WT 13 OZ (368 g)